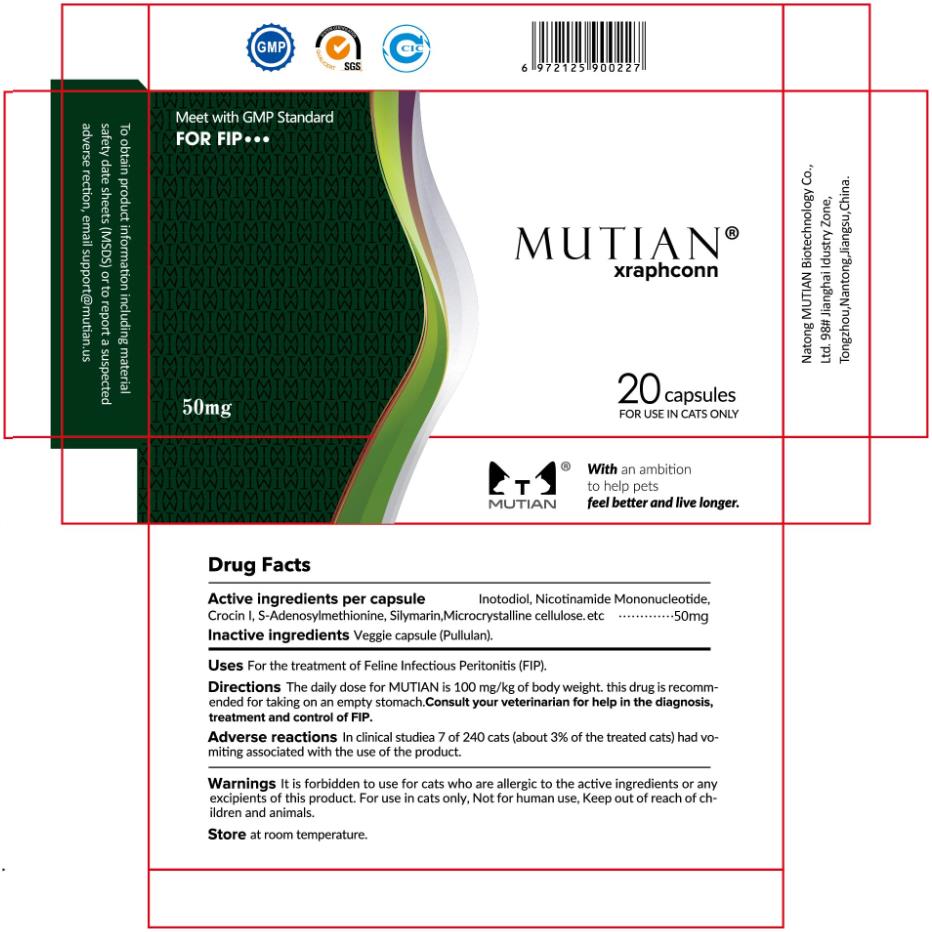 DRUG LABEL: MUTIAN Xraphconn
NDC: 73452-145 | Form: CAPSULE
Manufacturer: Nantong MUTIAN Biotechnology Co., Ltd
Category: animal | Type: OTC ANIMAL DRUG LABEL
Date: 20191203

ACTIVE INGREDIENTS: INONOTUS OBLIQUUS FRUITING BODY 2.5 mg/50 mg
INACTIVE INGREDIENTS: NICOTINAMIDE RIBOTIDE 7.5 mg/50 mg; CROCIN 5 mg/50 mg; S-ADENOSYLMETHIONINE SYNTHASE ISOFORM TYPE-2 3.75 mg/50 mg; MILK THISTLE 6.25 mg/50 mg; MICROCRYSTALLINE CELLULOSE 25 mg/50 mg

MuTian, Xraphconn, 50mg *20capsules

WARNINGS AND PRECAUTIONS

For cats use only, Not for human use.
Keep out of reach of children and animals.
It is forbidden to use for cats who are allergic to the active ingredients or any excipients of this products.

INDICATIONS AND USAGE

For the treatment of Feline Infectious Peritonitis (FIP).
Oral use.
This drug is recommended for taking on an empty stomach.
Consult your veterinarian for help in the diagnosis, treatment and control of FIP.

DOSAGE AND ADMINISTRATION

The daily dose for MUTIAN is 100mg/kg of body weight.

ACTIVE INGREDIENT

Inotodiol

INACTIVE INGREDIENT

Nicotinamide Mononucleotide
Crocin
S-Adenosylmethionine
Silymarin
Microcrystalline cellulose

ADVERSE REACTIONS

In clinical studies 7 of 240 cats (about 3% of the treated cats) had vomiting associated with the use of the product.

Keep out of reach of children and animals.

STORAGE AND HANDLING

Store at the room temperature.

Outer Package